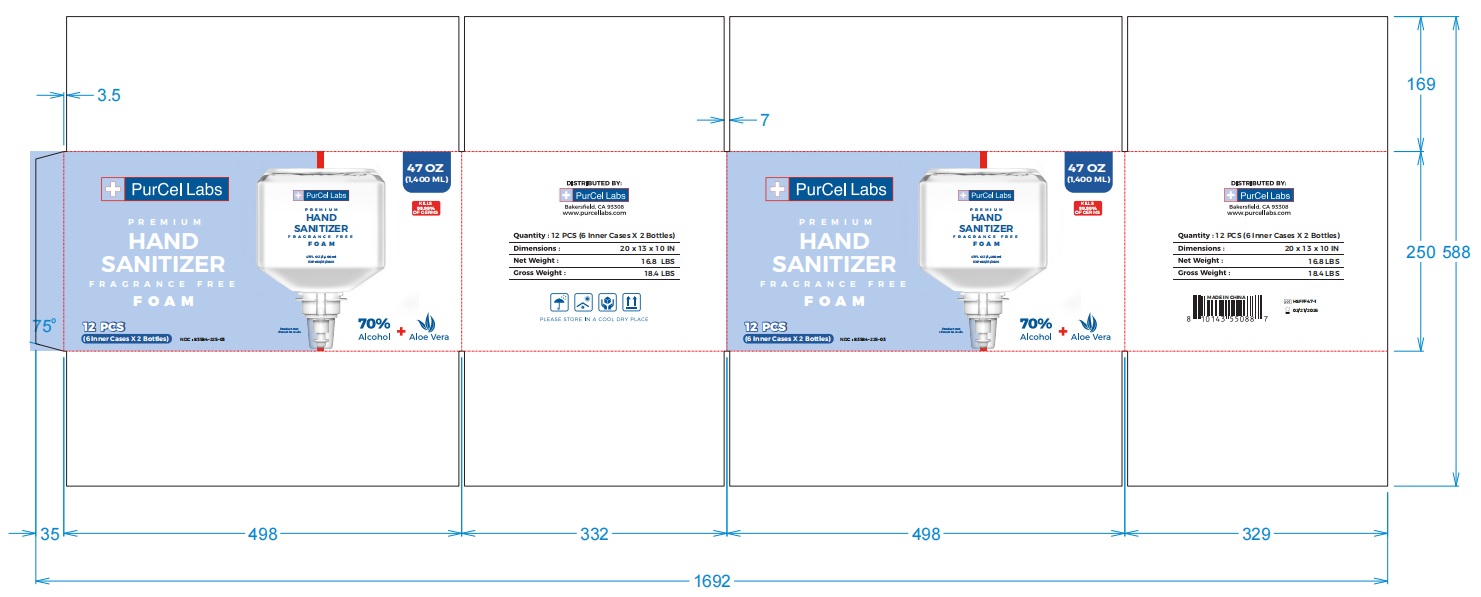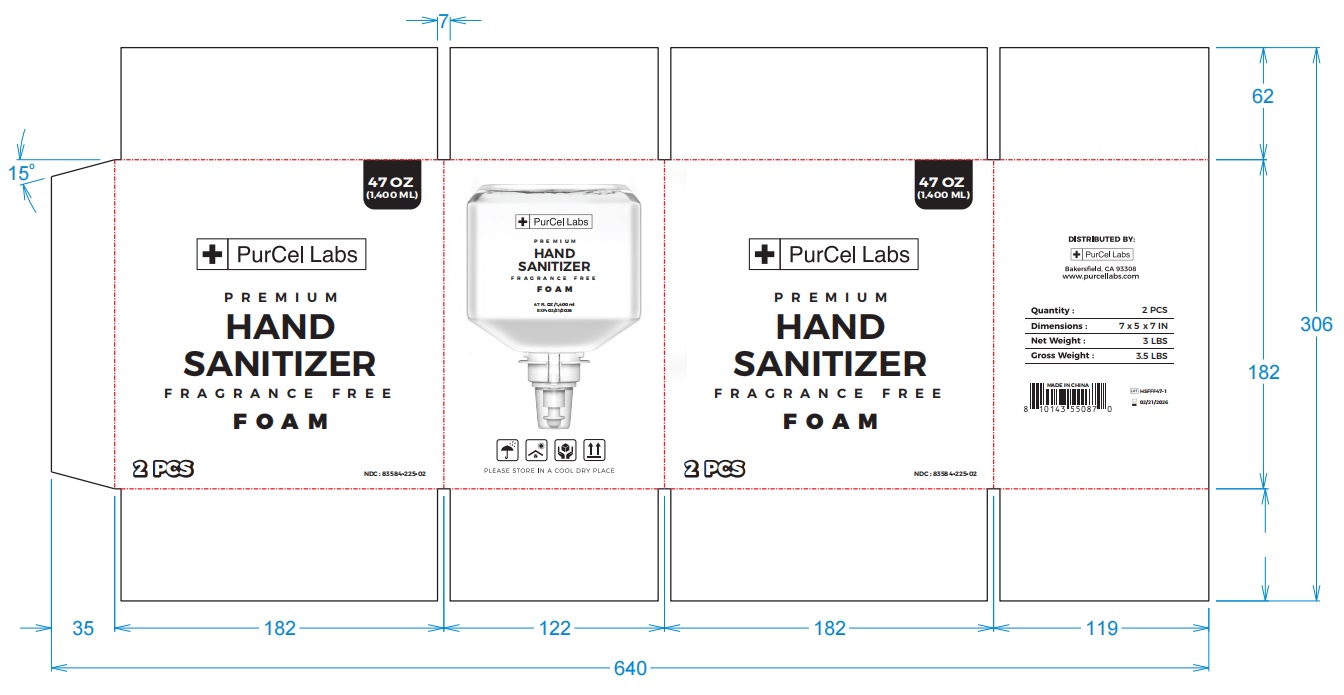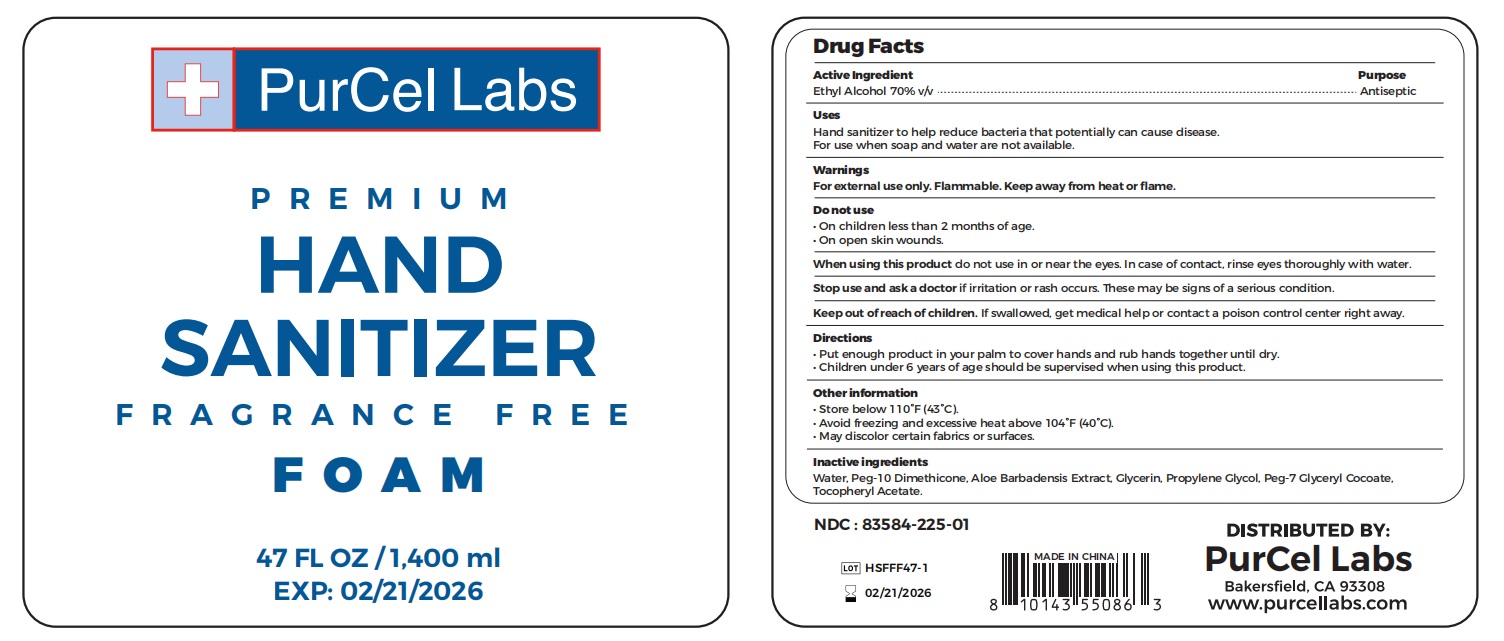 DRUG LABEL: Hand Sanitizer FOAM
NDC: 83584-225 | Form: AEROSOL, FOAM
Manufacturer: PurCel Labs LLC
Category: otc | Type: HUMAN OTC DRUG LABEL
Date: 20240305

ACTIVE INGREDIENTS: ALCOHOL 70 mL/100 mL
INACTIVE INGREDIENTS: PROPYLENE GLYCOL; WATER; PEG-10 DIMETHICONE (600 CST); ALOE VERA LEAF; PEG-7 GLYCERYL COCOATE; GLYCERIN; ALPHA-TOCOPHEROL ACETATE

Active Ingredient

Ethyl Alcohol 70% v/v

Purpose

Antiseptic

Uses

Hand sanitizer to help reduce bacteria that potentially can cause disease.
For use when soap and water are not available.

Warnings

For external use only. Flammable. Keep away from heat or flame.

Do not use

• On children less than 2 months of age.
• On open skin wounds.

When using this product do not use in or near the eyes. In case of contact, rinse eyes thoroughly with water.

Stop use and ask a doctor if irritation or rash occurs. These may be signs of a serious condition.

Keep out of reach of children. If swallowed, get medical help or contact a poison control center right away.

Directions

• Put enough product in your palm to cover hands and rub hands together until dry.
• Children under 6 years of age should be supervised when using this product.

Other information

• Store below 110°F (43°C).
• Avoid freezing and excessive heat above 104°F (40°C).
• May discolor certain fabrics or surfaces.

Inactive ingredients

Water, Peg-10 Dimethicone, Aloe Barbadensis Extract, Glycerin, Propylene Glycol, Peg-7 Glyceryl Cocoate,
Tocopheryl Acetate.